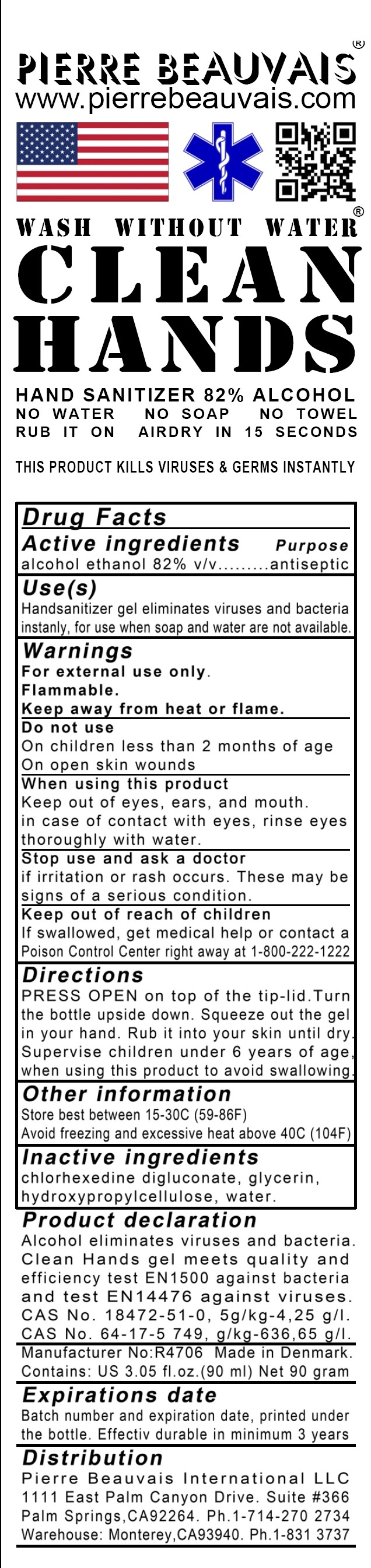 DRUG LABEL: Clean Hands Wash Without Water
NDC: 79908-001 | Form: GEL
Manufacturer: Pierre Beauvais A/S
Category: otc | Type: HUMAN OTC DRUG LABEL
Date: 20201019

ACTIVE INGREDIENTS: ALCOHOL 82 mL/100 mL
INACTIVE INGREDIENTS: WATER; HYDROXYPROPYL CELLULOSE (1200000 WAMW); CHLORHEXIDINE GLUCONATE; GLYCERIN

Active ingredient

Ethyl alcohol 82%

DOSAGE AND ADMINISTRATION

Rub Clean Hands onto hands and skin

Purpose

82% alcohol kills 99,9% of all bacteria, fungals spurs, germs and viruses instantly, like hepatitis, H1N1, SARS and HIV virus infections. Eliminate pain from goplers and insect sting/bites.

Use

Use it all day. Added chlorhexidine for disinfection. SOAP DO NOT KILL VIRUS. CLEAN HANDS DOES

Caution:

Danger: Highly inflammable until evaporated Must be stored under 43oC/108oF. For external use only. Avoid contact with ears and eyes, or flush thoroughly with water. Keep out of reach of children

Inactive ingredients

Water (Aqua). Hydroxypropylcellulose. Glycerin, Chlorhexidine Digluconate.